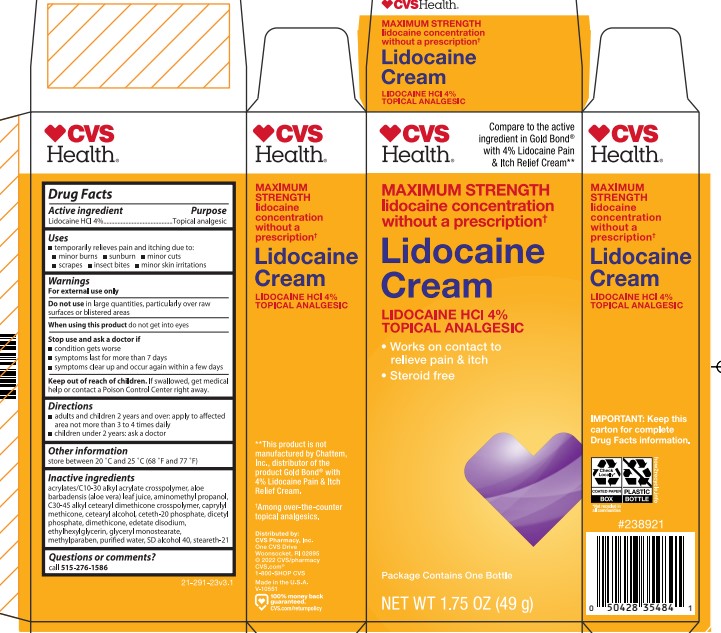 DRUG LABEL: CVS Lidocaine
NDC: 69842-921 | Form: CREAM
Manufacturer: CVS Pharmacy
Category: otc | Type: HUMAN OTC DRUG LABEL
Date: 20251203

ACTIVE INGREDIENTS: LIDOCAINE HYDROCHLORIDE 4 g/100 g
INACTIVE INGREDIENTS: CAPRYLYL METHICONE; WATER; AMINOMETHYLPROPANOL; DIMETHICONE; STEARETH-21; METHYLPARABEN; CETEARYL ALCOHOL; CETETH-20 PHOSPHATE; DICETYL PHOSPHATE; GLYCERYL MONOSTEARATE; ACRYLATES/C10-30 ALKYL ACRYLATE CROSSPOLYMER (60000 MPA.S); ALOE VERA LEAF; EDETATE DISODIUM; ETHYLHEXYLGLYCERIN; ALCOHOL; C30-45 ALKYL CETEARYL DIMETHICONE CROSSPOLYMER

CVS Lidocaine HCl Cream

ACTIVE INGREDIENT

Lidocaine HCl 4%

PURPOSE

Topical analgesic

Uses

temporarily relieves pain and itching due to:

- minor burns
- sunburn
- minor cuts
- scrapes
- insect bites
- minor skin irritations

WARNINGS

For external use only

Do not use in large quantities, particularly over raw surfaces or blistered areas

When using this product do not get into eyes

Stop use and ask a doctor if

- condition gets worse
- symptoms last for more than 7 days
- symptoms clear up and occur again within a few days

Keep out of reach of children. If swallowed, get medical help or contact a Poison Control Center right away.

Directions

- adults and children 2 years and over: apply to affected area not more than 3 to 4 times daily
- children under 2 years: ask a doctor

Other information

store between 20 °C and 25 °C (68 °F and 77 °F)

INACTIVE INGREDIENT

acrylates/C10-30 alkyl acrylate crosspolymer, aloe barbadensis (aloe vera) leaf juice, aminomethyl propanol,
C30-45 alkyl cetearyl dimethicone crosspolymer, caprylyl methicone, cetearyl alcohol, ceteth-20 phosphate, dicetyl phosphate, dimethicone, edetate disodium, ethylhexylglycerin, glyceryl monostearate, methylparaben, purified water, SD alcohol 40, steareth-21

PACKAGE LABEL

CVS Health

Multi- Symptom Formula Works On Contact to relieve Pain & Itch From:

Minor Burns & cuts

Minor Skin Irritaions

Insect bites

Sunburns

Maximum Strength Lidocaine Cream Lidocaine HCL 4 %- Topical Analgesic

Steroid free, Works on Contact